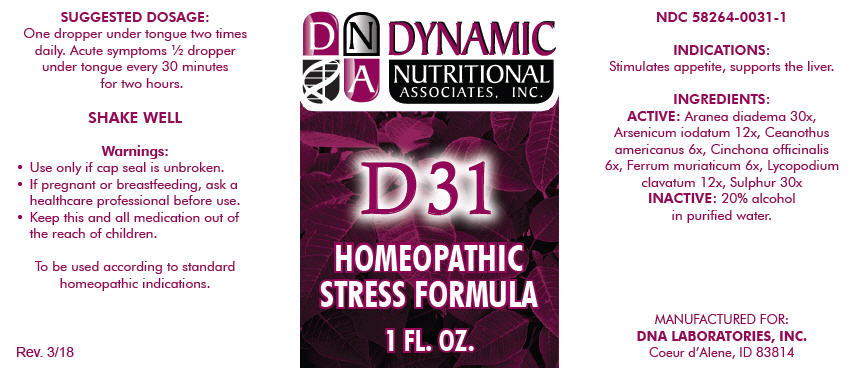 DRUG LABEL: D-31
NDC: 58264-0031 | Form: SOLUTION
Manufacturer: DNA Labs, Inc.
Category: homeopathic | Type: HUMAN OTC DRUG LABEL
Date: 20250113

ACTIVE INGREDIENTS: ARANEUS DIADEMATUS 30 [hp_X]/1 mL; ARSENIC TRIIODIDE 12 [hp_X]/1 mL; CEANOTHUS AMERICANUS LEAF 6 [hp_X]/1 mL; CINCHONA OFFICINALIS BARK 6 [hp_X]/1 mL; FERRIC CHLORIDE HEXAHYDRATE 6 [hp_X]/1 mL; LYCOPODIUM CLAVATUM SPORE 12 [hp_X]/1 mL; SULFUR 30 [hp_X]/1 mL
INACTIVE INGREDIENTS: ALCOHOL; WATER

D-31

NDC 58264-0031-1

INDICATIONS

PURPOSE

Stimulates appetite, supports the liver.

INGREDIENTS

ACTIVE

Aranea diadema 30x, Arsenicum iodatum 12x, Ceanothus americanus 6x, Cinchona officinalis 6x, Ferrum muriaticum 6x, Lycopodium clavatum 12x, Sulphur 30x

INACTIVE

20% alcohol in purified water.

SUGGESTED DOSAGE

One dropper under tongue two times daily. Acute symptoms ½ dropper under tongue every 30 minutes for two hours.

STORAGE AND HANDLING

SHAKE WELL

Warnings

- Use only if cap seal is unbroken.

PREGNANCY OR BREAST FEEDING

- If pregnant or breastfeeding, ask a healthcare professional before use.

KEEP OUT OF REACH OF CHILDREN

- Keep this and all medication out of the reach of children.

To be used according to standard homeopathic indications.

PRINCIPAL DISPLAY PANEL - 1 FL. OZ. Bottle Label

DYNAMIC
NUTRITIONAL
ASSOCIATES, INC.

D 31

HOMEOPATHIC
STRESS FORMULA

1 FL. OZ.